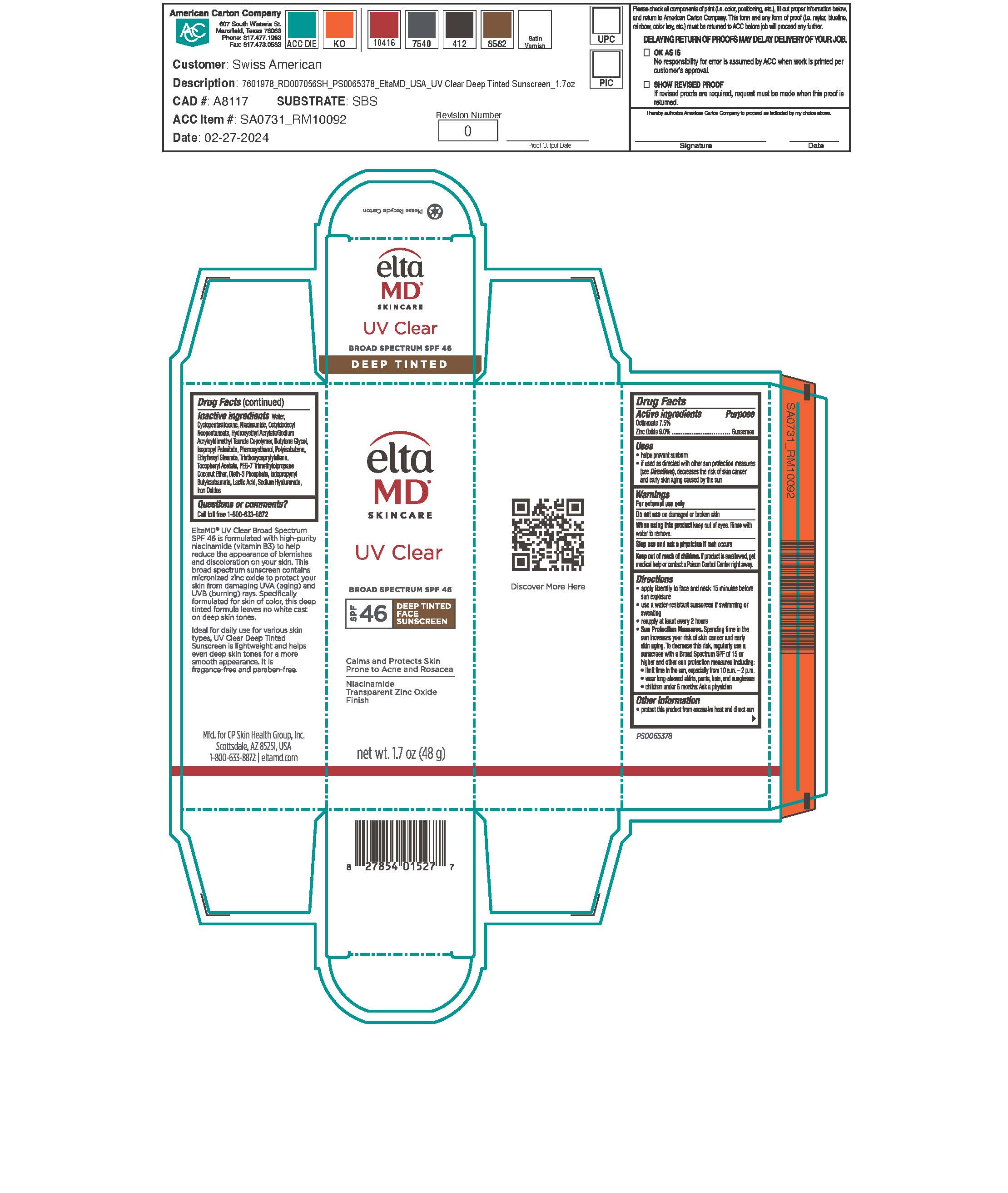 DRUG LABEL: UV Clear Deep Tint
NDC: 72043-2530 | Form: LOTION
Manufacturer: CP Skin Health Group, Inc.
Category: otc | Type: HUMAN OTC DRUG LABEL
Date: 20240508

ACTIVE INGREDIENTS: OCTINOXATE 750 g/1000 g; ZINC OXIDE 900 g/1000 g
INACTIVE INGREDIENTS: WATER; BUTYLENE GLYCOL; PHENOXYETHANOL; IODOPROPYNYL BUTYLCARBAMATE; LACTIC ACID; HYALURONIC ACID; NIACINAMIDE; ISOPROPYL PALMITATE; ETHYLHEXYL STEARATE; OCTYLDODECYL NEOPENTANOATE; OLETH-3 PHOSPHATE; PHOSPHORIC ACID; FERRIC OXIDE YELLOW; FERRIC OXIDE RED; FERROSOFERRIC OXIDE; CYCLOMETHICONE 5; BUTYLATED HYDROXYTOLUENE; .ALPHA.-TOCOPHEROL ACETATE; TRIETHOXYCAPRYLYLSILANE; HYDROXYETHYL ACRYLATE/SODIUM ACRYLOYLDIMETHYL TAURATE COPOLYMER (45000 MPA.S AT 1%); POLYISOBUTYLENE (1000 MW); PEG-7 TRIMETHYLOLPROPANE COCONUT ETHER

EltaMD UV Clear Deep Tint

Warnings

For external use only. Do not use on damaged or broken skin. When using this product keep out of eyes. Rinse with water to remove. Stop use and ask a physician if rash occurs. If product is swallowed get medical help or contact a Poison Control Center right away.

Keep out of reach of children

Uses

Helps prevent sunburn. If used as directed with other sun protection measure (See Directions), decreases the risk of skin cancer and early skin aging caused by the sun.

Uses

Helps prevent sunburn. If used as directed with other sun protection measure (See Directions), decreases the risk of skin cancer and early skin aging caused by the sun.

Directions

Apply liberally 15 minutes before sun exposure. Use a water-resistant sunscreen if swimming or sweating. Reapply at least every 2 hours. Sun Protection Measures: Spending time in the sun increases your risk of skin cancer and early skin aging. To decrease this risk, regularly use a sunscreen with a broad-spectrum SPF of 15 or higher and other sun protection measures including: limit time in the sun, especially from 10 am to 2 pm. Wear long-sleeve shirts, pants, hats, and sunglasses. Children under 6 months: ask a physician.

Active Ingredients

Octinoxate 7.5%

Zinc Oxide 9.0%

Inactive Ingredients

water, cyclopentasiloxane, niacinamide, octyldodecyln eopentanoate, hydroxyethyl acrylate/sodium acryloldimethyl taurate copolymer, butylee glycol, isopropyl palmitate, phenoxyethanol, polyisobutene, ethylheyl stearate, triethoxycaprylylsilane, tocopheryl acetate, PEG-7 trimethylolpropane coconut ether, oleth-3 phosphate, iodopropynyl butylcarbamate, latic acid, sodiym hyaluroate, iron oxides

Questions

Call toll free 1-800-633-8872